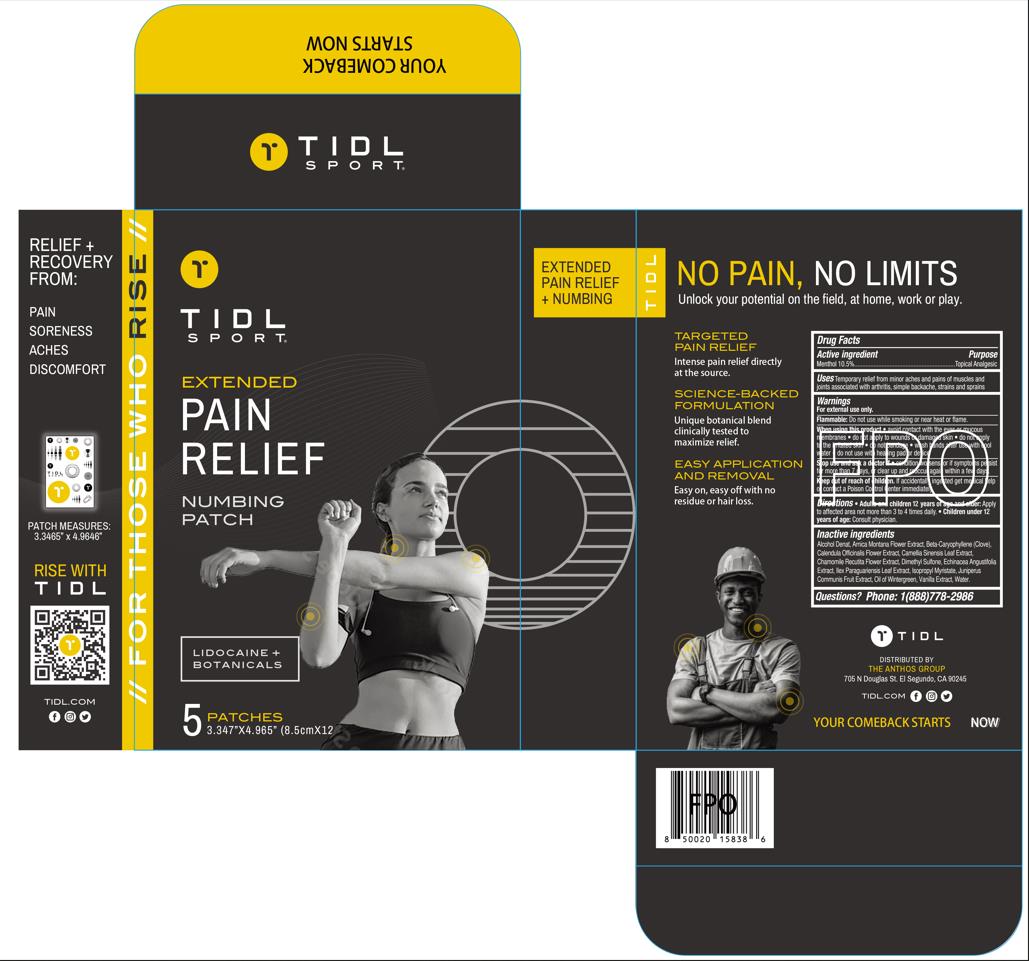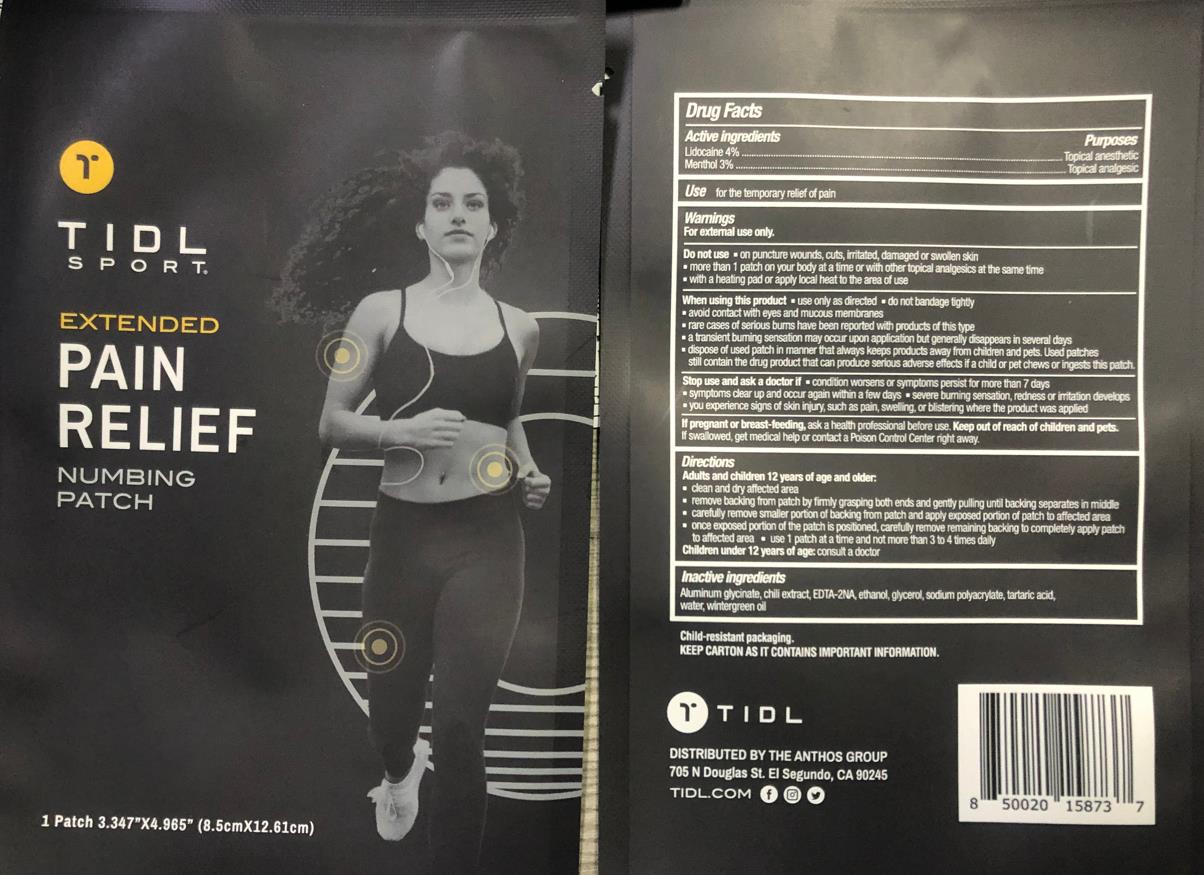 DRUG LABEL: TIDL PAIN RELIEF NUMBING
NDC: 79740-009 | Form: PATCH
Manufacturer: The Anthos Group
Category: otc | Type: HUMAN OTC DRUG LABEL
Date: 20240221

ACTIVE INGREDIENTS: MENTHOL 3 g/100 1; LIDOCAINE 4 g/100 1
INACTIVE INGREDIENTS: GLYCERIN; SODIUM POLYACRYLATE (2500000 MW); METHYL SALICYLATE; ALCOHOL; TARTARIC ACID; DIHYDROXYALUMINUM AMINOACETATE ANHYDROUS; CAPSICUM; WATER; EDETIC ACID

79740-009 更新信息
TIDL PAIN RELIEF NUMBING PATCH

ACTIVE INGREDIENT

Lidocaine 4%,

Menthol 3%

PURPOSE

Topical Analgesic

INDICATIONS AND USAGE

Uses Temporary relief from minor aches and pains of muscles and joints associated with arthritis, simple backache, strains and sprains

WARNINGS

Wamings
For extemal use only .
Do not use a on puncture wounds , cuts , imitated , damaged or swollen skin
more than 1 path on your body at a time or with other topical analgesics at the same time
with a heating pad or apply local heat to the area of use
When using his product
use only as directed
do not bandage tighty
avoid contact with eyes and mucous membranes
rare cases of serous bums have been reported with products of this type
a transient buming sensation may occur upon application but enerally disappears in several days
dispose of used patch in manner hat always keeps products away from children and pets . Used patches still contain e g po at can po s ad fs f a hid or pt chews or ingests this patch
Stop use and ask a doctor if condition worsens or symptoms persist for more than 7 days
symptoms ear up and occur again within a few days
severe burning sensation, redness or irritation develops
you experience signs of skin inur , such as pain , sw , or blistering where the product was appliedIf pregnant or breast-feeing , ask a health professional efore use . ep out of each of hilden .If swallowed , get medical help or contact a Poison Control Center night away

INACTIVE INGREDIENT

Purity Water, 059QF0KO0R
Glycerol, PDC6A3C0OX
Sodium polyacrylate, 05I15JNI2J
Wintergreen Oil, LAV5U5022Y
Ethanol, 3K9958V90M
Tartaric acid, W4888I119H
Aluminum Glycinate, 1K713C615K
Chilli extract, 00UK7646FG
EDTA-2NA, 9G34HU7RV0

DOSAGE AND ADMINISTRATION

one slice at a time

PACKAGE LABEL

79740-009-1 5 BAG in 1 BOX

79740-009-2 1 PATCH in 1 BAG